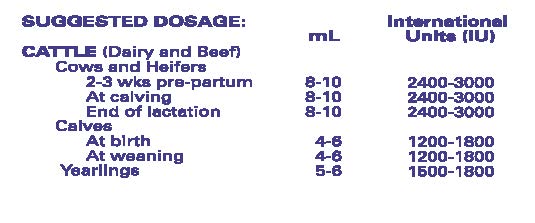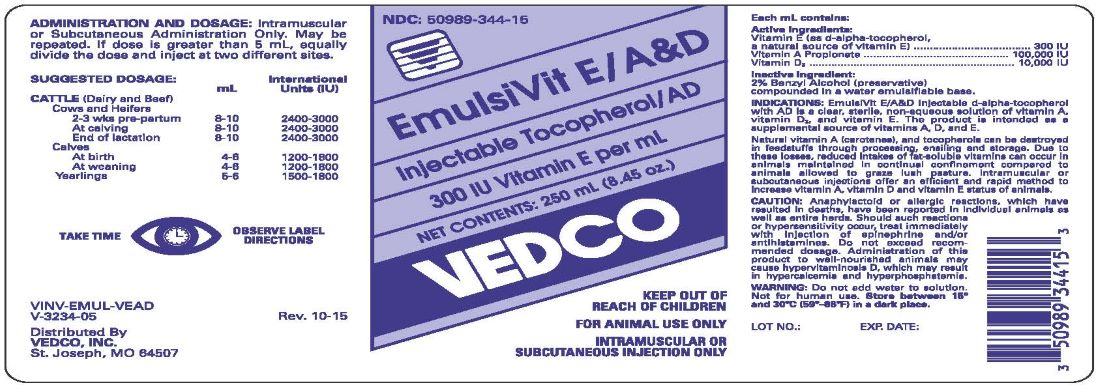 DRUG LABEL: EmulsiVit E AD
NDC: 50989-344 | Form: INJECTION
Manufacturer: Vedco, Inc.
Category: animal | Type: OTC ANIMAL DRUG LABEL
Date: 20231211

ACTIVE INGREDIENTS: .ALPHA.-TOCOPHEROL, D- 201 mg/1 mL; VITAMIN A 3.6 mg/1 mL; VITAMIN D 2.5 mg/1 mL

EmulsiVit E/A&D

INDICATIONS AND USAGE

EmulsiVit E/A&D

Injectable Tocopherol/AD

Indications: EmulsiVitE/A&D Injectable d-alpha tocopherol with AD is a clear, sterile, non-aqueous solution of vitamin A,vitamin D3,and vitamin E. The product is intended as a supplemental source of vitamins A, D and E.

Natural vitamin A (carotenes), and tocopherols can be destroyed in feedstuffs through processing, ensiling and storage. Due to these losses, reduced intakes of fat-soluble vitamins can occur in animals maintained in continual confinement compared to animals allowed to graze in lush pasture. Intramuscular or subcutaneous injections offer an efficient and rapid method to increase vitamin A, vitamin D and Vitamin E status of animals.

Each mL contains:

Active Ingredients:

vitamin E (as d-alpha-tocopherol,

a natural source of vitamin E).....................................300 IU

Vitamin A Propionate...........................................100,000 IU

Vitamin D3...........................................................10,000 IU

Inactive Ingredients: 2% benzyl alcohol (preservative)

compounder in a water emulsifiable base.

Caution:

Anaphylactoid or allergic reactions, which have resulted in deaths, have been reported in individual animals as well as entire herds. Should such reactions or hypersensitivity occur, treat immediately with injection of epinephrine and/or antihistamines. Do not exceed recomended dosage. Administration of this product to well-nourished animals may cause hypervitaminosis D, which may result in hypercalcemia and hyperphosphatemia.

Warning:

Do not add water to solution.

Not for human use.

STORAGE AND HANDLING

Store between 15°—30°C (59°—86°F) in a dark place

ADMINISTRATION AND DOSAGE:

Intramuscular or Subcutaneous Administration Only. May be repeated. If dose is greater than 5 mL, equally divide the dose and inject at two sites.